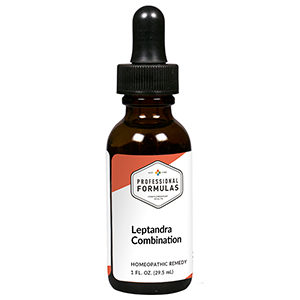 DRUG LABEL: Leptandra Combination
NDC: 63083-9230 | Form: LIQUID
Manufacturer: Professional Complementary Health Formulas
Category: homeopathic | Type: HUMAN OTC DRUG LABEL
Date: 20190815

ACTIVE INGREDIENTS: VERONICASTRUM VIRGINICUM WHOLE 2 [hp_X]/29.5 mL; QUASSIA AMARA WOOD 3 [hp_X]/29.5 mL; VERATRUM ALBUM ROOT 4 [hp_X]/29.5 mL; ARSENIC TRIOXIDE 6 [hp_X]/29.5 mL; CEANOTHUS AMERICANUS LEAF 6 [hp_X]/29.5 mL; LYCOPODIUM CLAVATUM SPORE 6 [hp_X]/29.5 mL; MOMORDICA BALSAMINA WHOLE 6 [hp_X]/29.5 mL; PHOSPHORUS 6 [hp_X]/29.5 mL; PODOPHYLLUM 6 [hp_X]/29.5 mL; IODINE 8 [hp_X]/29.5 mL; MANDRAGORA OFFICINARUM ROOT 8 [hp_X]/29.5 mL; ACTIVATED CHARCOAL 10 [hp_X]/29.5 mL; NICKEL 10 [hp_X]/29.5 mL; SILVER NITRATE 12 [hp_X]/29.5 mL; MERCURIUS SOLUBILIS 12 [hp_X]/29.5 mL
INACTIVE INGREDIENTS: ALCOHOL; WATER

R230

ACTIVE INGREDIENTS

Leptandra virginica 2X
Quassia amara 3X
Veratrum album 4X
Arsenicum album 6X
Ceanothus americanus 6X
Lycopodium clavatum 6X
Momordica balsamina 6X
Phosphorus 6X
Podophyllum peltatum 6X
Iodium 8X
Mandragora officinarum 8X
Carbo vegetabilis 10X
Niccolum metallicum 10X
Argentum nitricum 12X
Mercurius solubilis 12X

QUESTIONS

Professional Formulas

PO Box 2034 Lake Oswego, OR 97035

INDICATIONS

For the temporary relief of diarrhea, stomach or abdominal cramping, flatulence, nausea, or vomiting.*

PURPOSE

*Claims based on traditional homeopathic practice, not accepted medical evidence. Not FDA evaluated.

WARNINGS

If symptoms do not improve or are accompanied by a fever, consult a doctor. Keep out of the reach of children. In case of overdose, get medical help or contact a poison control center right away. If pregnant or breastfeeding, ask a healthcare professional before use.

Keep out of the reach of children.

PREGNANCY OR BREAST FEEDING

If pregnant or breastfeeding, ask a healthcare professional before use.

DIRECTIONS

Place drops under tongue 30 minutes before/after meals. Adults and children 12 years and over: Take 10 drops up to 3 times per day. Consult a physician for use in children under 12 years of age.

OTHER INFORMATION

Tamper resistant. If seal is broken, do not use. After opening, close container tightly and store at room temperature away from heat.

INACTIVE INGREDIENTS

40% ethanol, purified water.

LABEL

Est 1985

Professional Formulas

Complementary Health

Leptandra Combination

Homeopathic Remedy

1 FL. OZ. (29.5 mL)